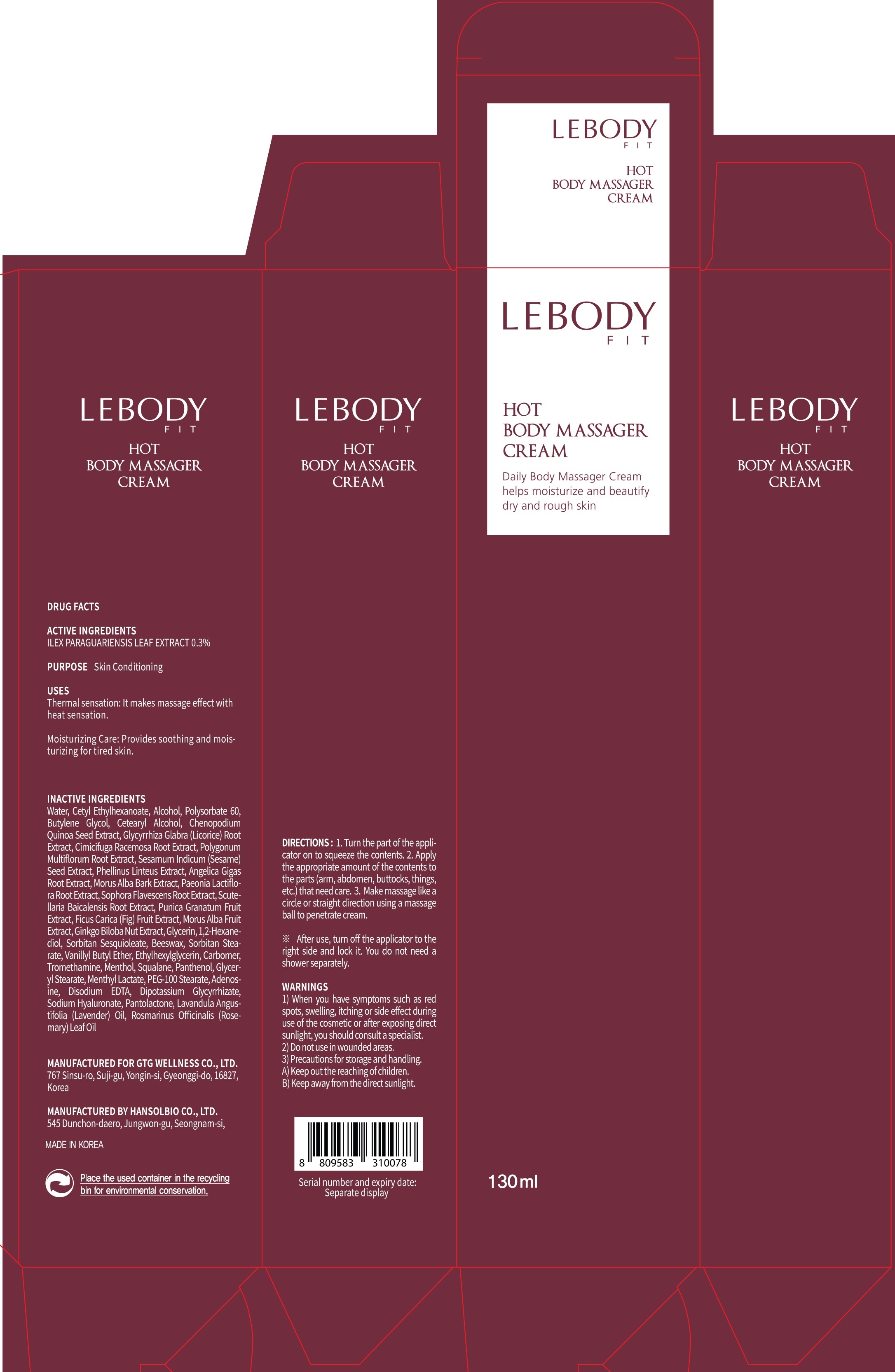 DRUG LABEL: LEBODY FIT HOT BODY MASSAGER
NDC: 71080-0006 | Form: CREAM
Manufacturer: GTG Wellness Co., Ltd.
Category: otc | Type: HUMAN OTC DRUG LABEL
Date: 20180208

ACTIVE INGREDIENTS: ILEX PARAGUARIENSIS LEAF 0.39 g/130 mL
INACTIVE INGREDIENTS: Water; Cetyl Ethylhexanoate

ACTIVE INGREDIENT

Active ingredients: ILEX PARAGUARIENSIS LEAF EXTRACT 0.3%

INACTIVE INGREDIENT

Inactive ingredients: Water, Cetyl Ethylhexanoate, Alcohol, Polysorbate 60, Butylene Glycol, Cetearyl Alcohol, Chenopodium Quinoa Seed Extract, Glycyrrhiza Glabra (Licorice) Root Extract, Cimicifuga Racemosa Root Extract, Polygonum Multiflorum Root Extract, Sesamum Indicum (Sesame) Seed Extract, Phellinus Linteus Extract, Angelica Gigas Root Extract, Morus Alba Bark Extract, Paeonia Lactiflora Root Extract, Sophora Flavescens Root Extract, Scutellaria Baicalensis Root Extract, Punica Granatum Fruit Extract, Ficus Carica (Fig) Fruit Extract, Morus Alba Fruit Extract, Ginkgo Biloba Nut Extract, Glycerin, 1,2-Hexanediol, Sorbitan Sesquioleate, Beeswax, Sorbitan Stearate, Vanillyl Butyl Ether, Ethylhexylglycerin, Carbomer, Tromethamine, Menthol, Squalane, Panthenol, Glyceryl Stearate, Menthyl Lactate, PEG-100 Stearate, Adenosine, Disodium EDTA, Dipotassium Glycyrrhizate, Sodium Hyaluronate, Pantolactone, Lavandula Angustifolia (Lavender) Oil, Rosmarinus Officinalis (Rosemary) Leaf Oil

PURPOSE

Purpose: Skin Conditioning

WARNINGS

Warnings: 1) When you have symptoms such as red spots, swelling, itching or side effect during use of the cosmetic or after exposing direct sunlight, you should consult a specialist. 2) Do not use in wounded areas. 3) Precautions for storage and handling. A) Keep out the reaching of children. B) Keep away from the direct sunlight.

KEEP OUT OF REACH OF CHILDREN

Uses

Thermal sensation: It makes massage effect with heat sensation.

Moisturizing Care: Provides soothing and moisturizing for tired skin.

Directions

1.Turn the part of the applicator on to squeeze the contents. 2.Apply the appropriate amount of the contents to the parts (arm, abdomen, buttocks, things, etc.) that need care. 3.Make massage like a circle or straight direction using a massage ball to penetrate cream.

*After use, turn off the applicator to the right side and lock it. You do not need a shower separately.